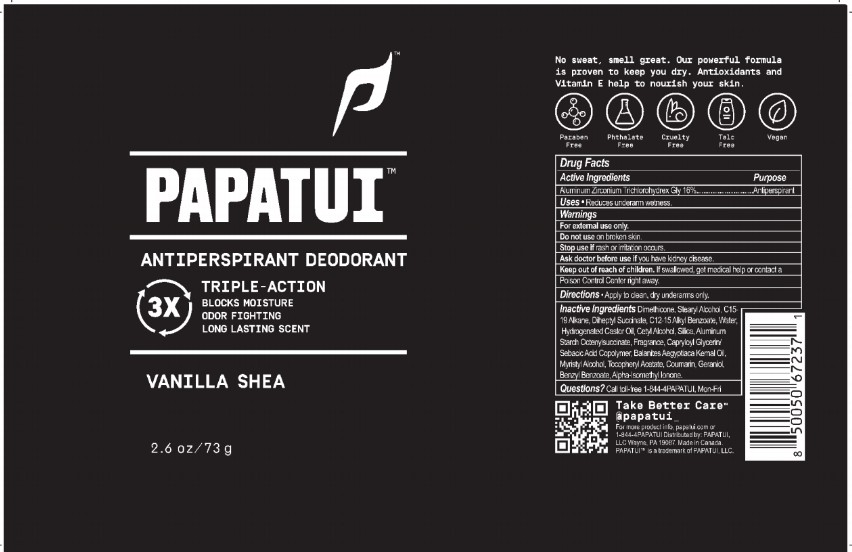 DRUG LABEL: Papatui Antiperspirant Deodorant Vanilla Shea
NDC: 83850-104 | Form: STICK
Manufacturer: PAPATUI LLC
Category: otc | Type: HUMAN OTC DRUG LABEL
Date: 20241211

ACTIVE INGREDIENTS: ALUMINUM ZIRCONIUM TRICHLOROHYDREX GLY 16 g/100 g
INACTIVE INGREDIENTS: ALPHA-ISOMETHYL IONONE; ALPHA-TOCOPHEROL ACETATE; CAPRYLOYL GLYCERIN/SEBACIC ACID COPOLYMER (2000 MPA.S); C15-19 ALKANE; DIMETHICONE; STEARYL ALCOHOL; GERANIOL; HYDROGENATED CASTOR OIL; SILICON DIOXIDE; DIHEPTYL SUCCINATE; C12-15 ALKYL BENZOATE; COUMARIN; WATER; BALANITES AEGYPTIACA SEED OIL; MYRISTYL ALCOHOL; BENZYL BENZOATE; CETYL ALCOHOL; ALUMINUM STARCH OCTENYLSUCCINATE

Papatui Antiperspirant Deodorant Vanilla Shea (NDC 83850-104)

DOSAGE AND ADMINISTRATION

PAPATUI

ANTI-PERSPIRANT DEODORANT

TRIPLE-ACTION

BLOCKS MOISTURE

ODOR FIGHTING

LONG LASTING SCENT

VANILLA SHEA

2.6 oz / 73 g

Drug Facts

Active Ingredient

Aluminum zirconium trichlorohydrex Gly 16%

Purpose

Antiperspirant

Use

Uses

Reduces underarm wetness

Warnings

For external use only.

Do not use on broken skin.

Stop use if rash or irritation occurs.

Ask doctor before use if you have kidney disease.

Keep out of reach of children. If swallowed, get medical help or contact a Poison Control Center right away.

Directions

Apply to clean, dry underarms only

Inactive Ingredients

Dimethicode, Stearyl Alcohol, C15-19 Alkane, Diheptyl Succinate, C12-15 Alkyl Benzoate, Water, Hydrogenated Castor Oil, Cetyl Alcohol, Silica, Aluminum Starch Octenylsuccinate, Fragrance, Capryloyl Glycerin/Sebacic Acid Copolymer, Balanites Aegyptiaca Kernal Oil, Myristyl Alcohol, Tocopheryl Acetate, Coumarin, Geraniol, Benzyl Benzoate, Alpha-Isomethyl Ionone.

Questions

Call toll-free 1-844-4PAPATUI, Mon-Fri